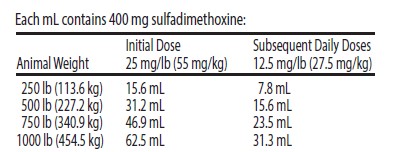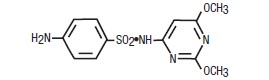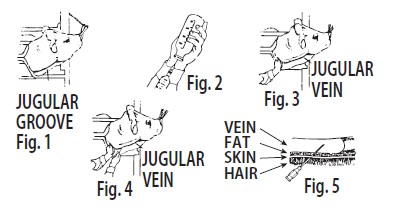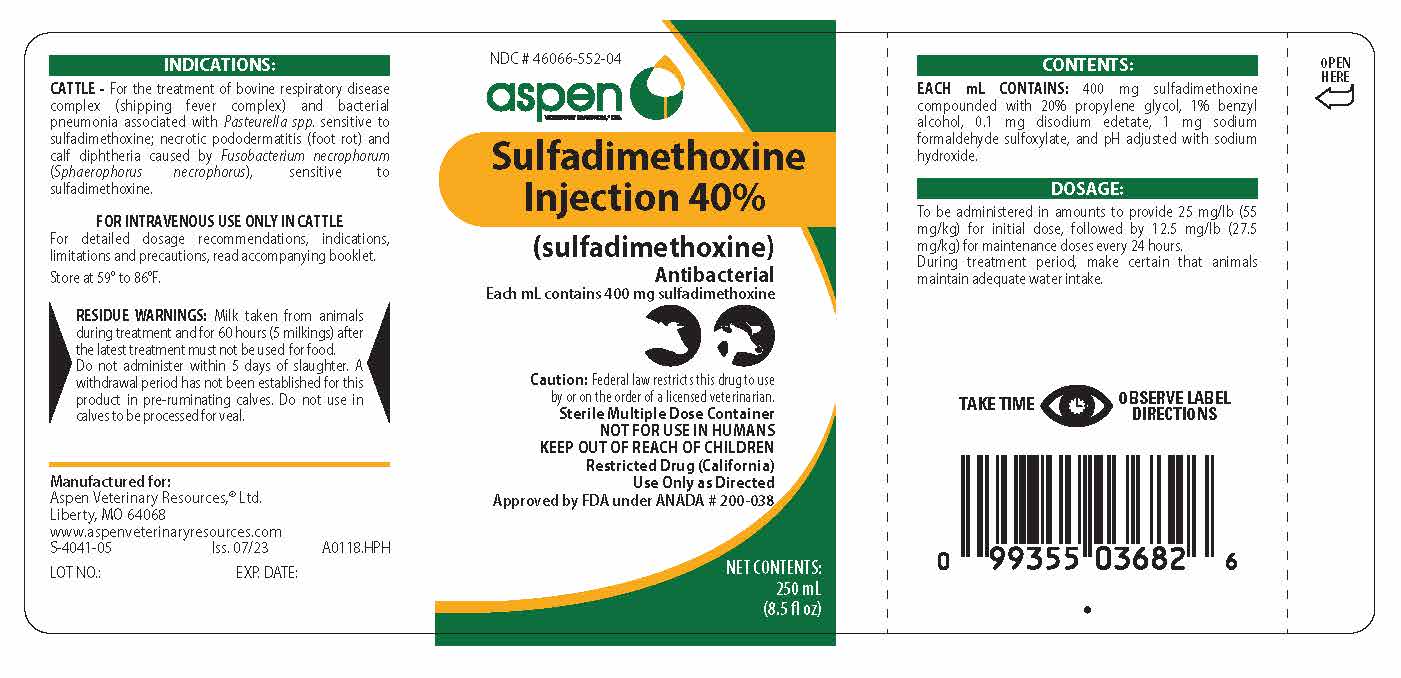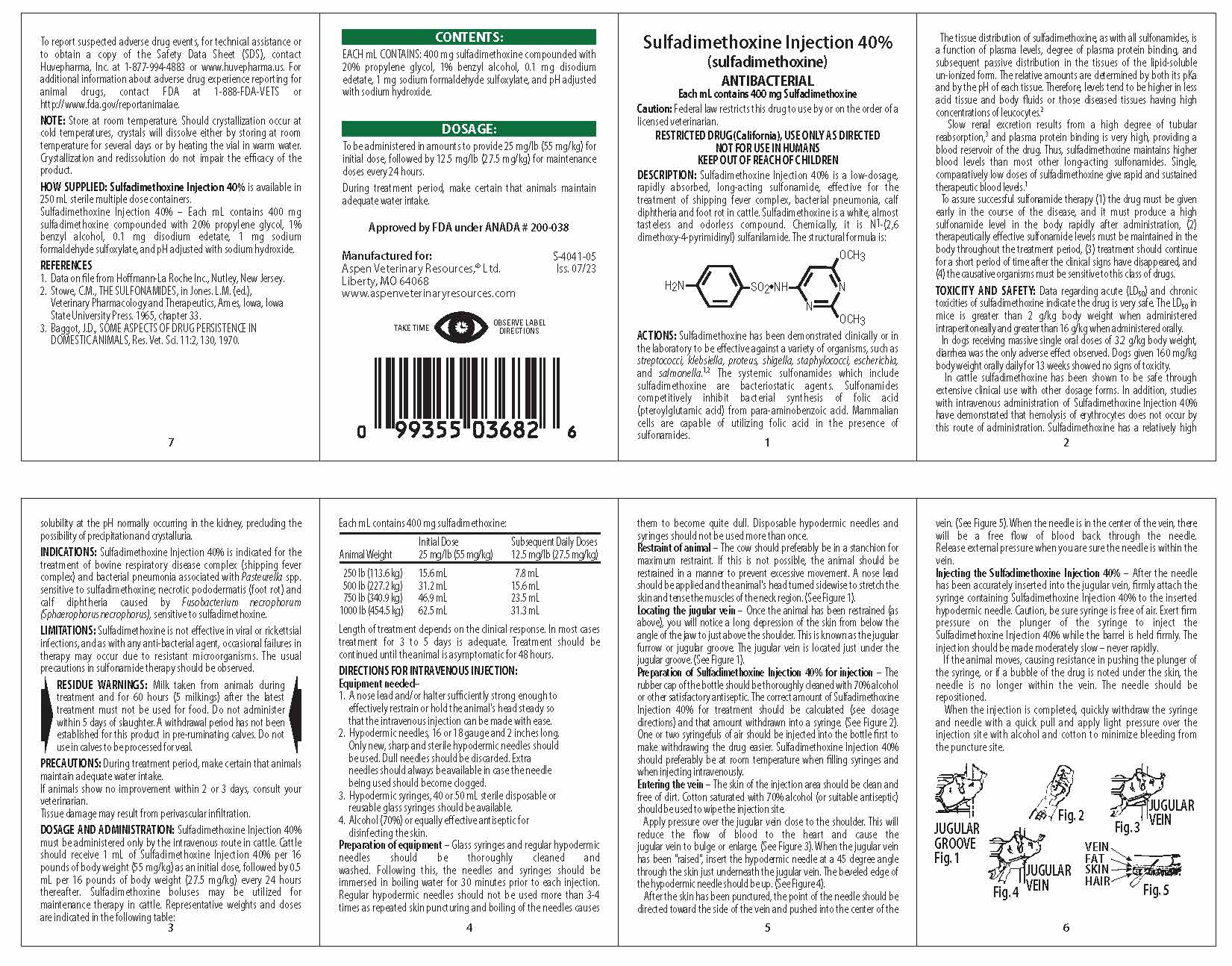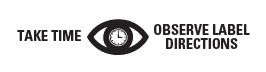 DRUG LABEL: SULFADIMETHOXINE
NDC: 46066-552 | Form: INJECTION
Manufacturer: Aspen Veterinary Resources, Ltd.
Category: animal | Type: PRESCRIPTION ANIMAL DRUG LABEL
Date: 20251114

ACTIVE INGREDIENTS: SULFADIMETHOXINE 400 mg/1 mL
INACTIVE INGREDIENTS: BENZYL ALCOHOL; EDETATE DISODIUM; PROPYLENE GLYCOL; SODIUM FORMALDEHYDE SULFOXYLATE; SODIUM HYDROXIDE; water

DESCRIPTION

Sulfadimethoxine Injection 40%
(sulfadimethoxine)

ANTIBACTERIAL
Each mL contains 400 mg Sulfadimethoxine
Caution: Federal law restricts this drug to use by or on the order of a
licensed veterinarian.

RESTRICTED DRUG (California), USE ONLY AS DIRECTED
NOT FOR USE IN HUMANS
KEEP OUT OF REACH OF CHILDREN

DESCRIPTION: Sulfadimethoxine Injection 40% is a low-dosage, rapidly absorbed, long-acting sulfonamide, effective for the
treatment of shipping fever complex, bacterial pneumonia, calf diphtheria and foot rot in cattle. Sulfadimethoxine is a white,
almost tasteless and odorless compound. Chemically, it is N^1-(2,6 dimethoxy-4-pyrimidinyl) sulfanilamide. The structural
formula is:

CLINICAL PHARMACOLOGY

ACTIONS: Sulfadimethoxine has been demonstrated clinically or in the laboratory to be effective against a variety of organisms,
such as streptococci, klebsiella, proteus, shigella, staphylococci, escherichia, and salmonella.^1,2 The systemic sulfonamides which
include sulfadimethoxine are bacteriostatic agents. Sulfonamides competitively inhibit bacterial synthesis of folic acid (pteroylglutamic
acid) from para-aminobenzoic acid. Mammalian cells are capable of utilizing folic acid in the presence of sulfonamides.

The tissue distribution of sulfadimethoxine, as with all sulfonamides, is a function of plasma levels, degree of plasma protein binding,
and subsequent passive distribution in the tissues of the lipid-soluble un-ionized form. The relative amounts are determined by both
its pKa and by the pH of each tissue. Therefore, levels tend to be higher in less acid tissue and body fluids or those diseased tissues
having high concentrations of leucocytes.^2

Slow renal excretion results from a high degree of tubular reabsorption,^3 and plasmaprotein binding is very high, providing a
blood reservoir of the drug. Thus, sulfadimethoxine maintains higher blood levels than most other long-acting sulfonamides. Single,
comparatively low doses of sulfadimethoxine give rapid and sustained therapeutic blood levels.^1

To assure successful sulfonamide therapy (1) the drug must be given early in the course of the disease, and it must produce a high
sulfonamide level in the body rapidly after administration, (2) therapeutically effective sulfonamide levels must be maintained in the
body throughout the treatment period, (3) treatment should continue for a short period of time after the clinical signs have disappeared,
and (4) the causative organisms must be sensitive to this class of drugs.

CLINICAL STUDIES

TOXICITY AND SAFETY: Data regarding acute (LD50) and chronic toxicities of sulfadimethoxine indicate the drug is very safe.
The LD50 in mice is greater than 2 g/kg body weight when administered intraperitoneally and greater than 16 g/kg when
administered orally.
In dogs receiving massive single oral doses of 3.2 g/kg body weight, diarrhea was the only adverse effect observed. Dogs given
160 mg/kg body weight orally daily for 13 weeks showed no sign of toxicity.
In cattle sulfadimethoxine has been shown to be safe through extensive clinical use with other dosage forms. In addition, studies
with intravenous administration of Sulfadimethoxine Injection 40% have demonstrated that hemolysis of erythrocytes does not occur
by this route of administration. Sulfadimethoxine has a relatively high solubility at the pH normally occurring in the kidney, precluding
the possibility of precipitation and crystalluria.

INDICATIONS AND USAGE

INDICATIONS: Sulfadimethoxine Injection 40% is indicated for the treatment of bovine respiratory disease complex (shipping fever
complex) and bacterial pneumonia associated with Pasteurella spp. sensitive to sulfadimethoxine; necrotic pododermatis (foot rot)
and calf diphtheria caused by Fusobacterium necrophorum (Sphaerophorus necrophorus), sensitive to sulfadimethoxine.

LIMITATIONS: Sulfadimethoxine is not effective in viral or rickettsial infections, and as with any anti-bacterial agent, occasional
failures in therapy may occur due to resistant microorganisms. The usual precautions in sulfonamide therapy should be observed.

RESIDUE WARNING

RESIDUE WARNINGS: Milk taken from animals during treatment and for 60 hours (5 milkings) after the latest treatment must not
be used for food. Do not administer within 5 days of slaughter. A withdrawal period has not been established for this product in
pre-ruminating calves. Do not use in calves to be processed for veal.

PRECAUTIONS

PRECAUTIONS: During treatment period, make certain that animals maintain adequate water intake.
If animals show no improvement within 2 or 3 days, consult your veterinarian.
Tissue damage may result from perivascular infiltration.

DOSAGE AND ADMINISTRATION

DOSAGE AND ADMINSTRATION: Sulfadimethoxine Injection 40% must be administered only by the intravenous route in cattle.
Cattle should receive 1 mL of Sulfadimethoxine Injection 40% per 16 pounds of body weight (55 mg/kg) as an initial dose,
followed by 0.5 mL per 16 pounds of body weight (27.5 mg/kg) every 24 hours thereafter. Sulfadimethoxine boluses may be
utilized for maintenance therapy in cattle. Representative weights and doses are indicated in the following table:

Length of treatment depends on the clinical response. In most cases treatment for 3 to 5 days is adequate. Treatment should be
continued until the animal is asymptomatic for 48 hours.

INSTRUCTIONS FOR USE

DIRECTIONS FOR INTRAVENOUS INJECTION:
Equipment needed-
1. A nose lead and/or halter sufficiently strong enough to effectively restrain or hold the animal's head steady so that the intravenous
injection can be made with ease.
2. Hypodermic needles, 16 or 18 gauge and 2 inches long. Only new, sharp and sterile hypodermic needles should be used. Dull needles
should be discarded. Extra needles should always be available in case of the needle being used should become clogged.
3. Hypodermic syringes, 40 or 50 mL sterile disposable or reusable glass syringes should be available.
4. Alcohol (70%) or equally effective antiseptic for disinfecting the skin.
Preparation of equipment - Glass syringes and regular hypodermic needles should be thoroughly cleaned and washed. Following this, the
needles and syringes should be immersed in boiling water for 30 minutes prior to each injection. Regular hypodermic needles should not
be used more than 3-4 times as repeated skin puncturing and boiling of the needles causes them to become quite dull. Disposable
hypodermic needles and syringes should not be used more than once.
Restraint of animal - The cow should preferably be in a stanchion for maximum restraint. If this is not possible, the animal should be
restrained in a manner to prevent excessive movement. A nose lead should be applied and the animal's head turned sidewise to stretch
the skin and tense the muscles of the neck region. (See Figure 1).
Locating the jugular vein - Once the animal has been restrained (as above), you will notice a long depression of the skin from below
the angle of the jaw to just above the shoulder. This is known as the jugular furrow or jugular groove. The jugular vein is located
just under the jugular groove. (See Fig. 1).
Preparation of Sulfadimethoxine Injection 40% for injection - The rubber cap of the bottle should be thoroughly cleaned with 70% alcohol
or other satisfactory antiseptic. The correct amount of Sulfadimethoxine Injection 40% for treatment should be calculated (see dosage
directions) and that amount withdrawn into a syringe. (See Figure 2). One or two syringefuls of air should be injected into the bottle
first to make withdrawing the drug easier. Sulfadimethoxine Injection 40% should preferably be at room temperature when filling syringes
and when injecting intravenously.
Entering the vein - The skin of the injection area should be clean and free of dirt. Cotton saturated with 70% alcohol (or suitable
antiseptic) should be used to wipe the injection site.
Apply pressure over the jugular vein close to the shoulder. This will reduce the flow of blood to the heart and cause the jugular vein
to bulge or enlarge. (See Figure 3). When the jugular vein has been "raised", insert the hypodermic needle at a 45 degree angle through
the skin just underneath the jugular vein. The beveled edge of the hypodermic needle should be up. (See Figure 4).
After the skin has been punctured, the point of the needle should be directed toward the side of the vein and pushed into the center of
the vein. (See Figure 5). When the needle is in the center of the vein, there will be a free flow of blood back through the needle.
Release external pressure when you are sure the needle is within the vein.
Injecting the Sulfadimethoxine Injection 40% - After the needle has been accurately inserted into the jugular vein, firmly attach the
syringe containing Sulfadimethoxine Injection 40% to the inserted hypodermic needle. Caution, be sure syringe is free of air. Exert
firm pressure on the plunger of the syringe to inject the Sulfadimethoxine Injection 40% while the barrel is held firmly. The injection
should be made moderately slow - never rapidly.
If the animal moves, causing resistance in pushing the plunger of the syringe, or if a bubble of the drug is noted under the skin, the
needle is no longer within the vein. The needle should be repositioned.
When the injection is completed, quickly withdraw the syringe and needle with a quick pull and apply light pressure over the injection
site with alcohol and cotton to minimize bleeding from the puncture site.

ADVERSE REACTIONS

To report suspected adverse drug events, for technical assistance or to obtain a copy of the Safety Data Sheet (SDS), contact
Huvepharma, Inc. at 1-877-994-4883 or www.huvepharma.us. For additional information about adverse drug experience reporting
for animal drugs, contact FDA at 1-888-FDA-VETS or http://www.fda.gov/reportanimalae.

NOTE: Store at room temperature. Should crystallization occur at cold temperatures, crystals will dissolve either by storing in room
temperature for several days or by heating the vial in warm water. Crystallization and redissolution do not impair the efficacy of the
product.

HOW SUPPLIED

HOW SUPPLIED: Sulfadimethoxine Injection 40% is available in 250 mL sterile multiple dose containers.
Sulfadimethoxine Injection 40% – Each mL contains 400 mg sulfadimethoxine compounded with 20% propylene glycol, 1%
benzyl alcohol, 0.1 mg disodium edetate, 1 mg sodium formaldehyde sulfoxylate, and pH adjusted with sodium hydroxide.

REFERENCES
1. Data on file from Hoffmann-La Roche Inc., Nutley, New Jersey.
2. Stowe, C.M., THE SULFONAMIDES, in Jones. L.M. (ed.), Veterinary Pharmacology and Therapeutics, Ames, Iowa, Iowa State University Press. 1965, chapter 33.
3. Baggot, J.D., SOME ASPECTS OF DRUG PERSISTENCE IN DOMESTIC ANIMALS, Res. Vet. Sci. 11:2, 130, 1970

CONTENTS:
EACH mL CONTAINS: 400 mg sulfadimethoxine compounded with 20% propylene glycol, 1% benzyl alcohol, 0.1 mg disodium
edetate, 1 mg sodium formaldehyde sulfoxylate, and pH adjusted with sodium hydroxide.

DOSAGE:

To be administered in amounts to provide 25 mg/lb (55 mg/kg) for initial dose, followed by 12.5 mg/lb (27.5 mg/kg) for maintenance
doses every 24 hours.

During treatment period, make certain that animals maintain adequate water intake.

Approved by FDA under ANADA # 200-038

Manufactured for:
Aspen Veterinary Resources,® Ltd.
Liberty, MO 64068
www.aspenveterinaryresources.com